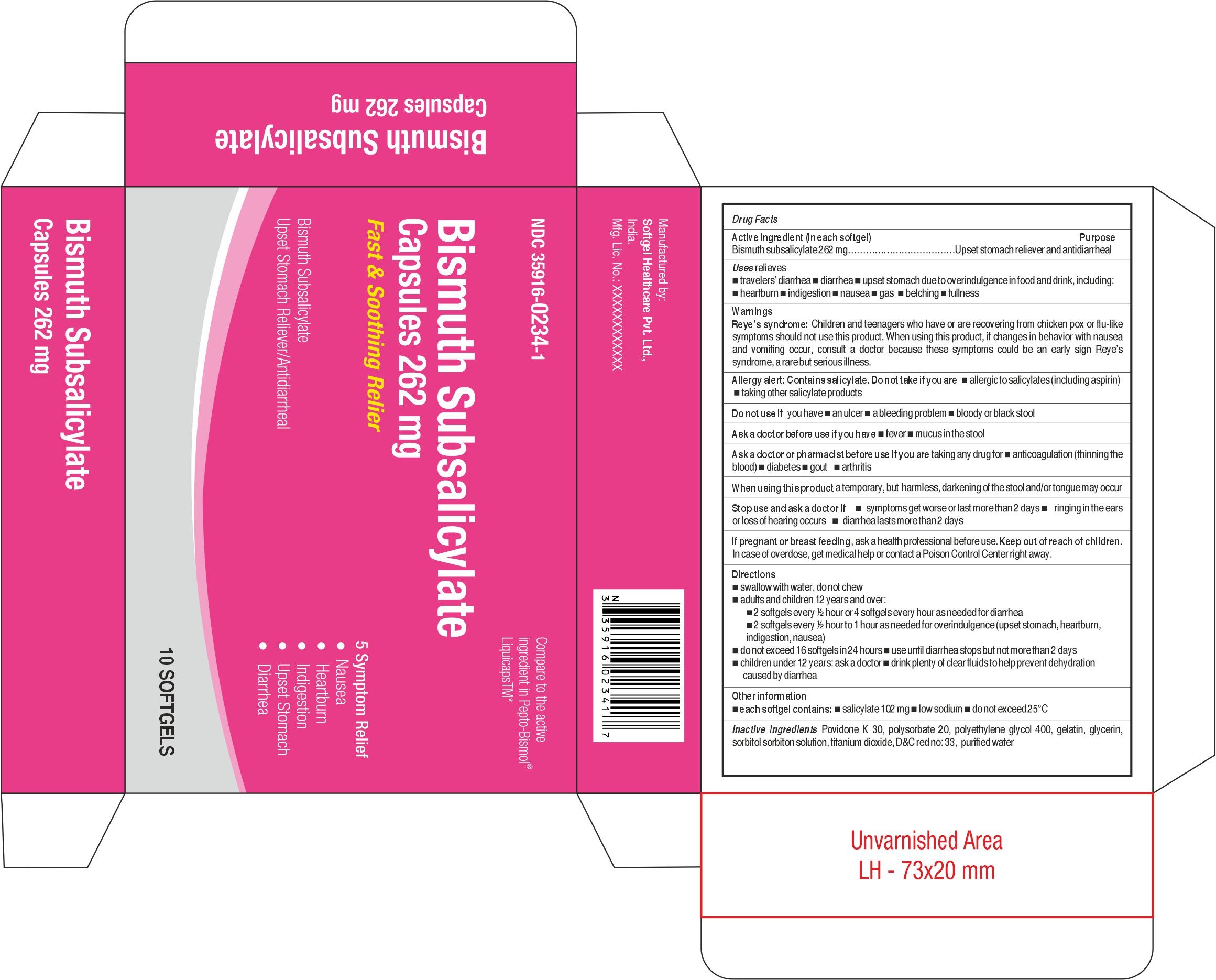 DRUG LABEL: Bismuth subsalicylate
NDC: 35916-0234 | Form: CAPSULE, LIQUID FILLED
Manufacturer: Softgel Healthcare Pvt Ltd
Category: otc | Type: HUMAN OTC DRUG LABEL
Date: 20260127

ACTIVE INGREDIENTS: BISMUTH SUBSALICYLATE 262 mg/1 1
INACTIVE INGREDIENTS: WATER; POLYSORBATE 20; SORBITOL; TITANIUM DIOXIDE; D&C RED NO. 33; GLYCERIN; POLYETHYLENE GLYCOL 400; GELATIN; POVIDONE

Bismuth Subsalicylate Capsules 262 mg

Active ingredient (in each softgel)

Bismuth subsalicylate 262 mg

Purpose

Upset stomach reliever and antidiarrheal

Uses

relieves

- travelers’ diarrhea
- diarrhea
- upset stomach due to overindulgence in food and drink, including:
- heartburn
- indigestion
- nausea
- gas
- belching
- fullness

Warnings Reye’s syndrome:

Children and teenagers who have or are recovering from chicken pox or flu-like symptoms should not use this product. When using this product, if changes in behavior with nausea and vomiting occur, consult a doctor because these symptoms could be an early sign Reye’s syndrome, a rare but serious illness.

Allergy alert:

Contains salicylate. Do not take if you are

- allergic to salicylates (including aspirin)
- taking other salicylate products

Do not use if

you have

- an ulcer
- a bleeding problem
- bloody or black stool

Ask a doctor before use if you have

- fever
- mucus in the stool

Ask a doctor or pharmacist before use if you are

taking any drug for

- anticoagulation (thinning the blood)
- diabetes
- gout
- arthritis

When using this product

a temporary, but harmless, darkening of the stool and/or tongue may occur

Stop use and ask a doctor if

- symptoms get worse or last more than 2 days
- ringing in the ears or loss of hearing occurs
- diarrhea lasts more than 2 days

If pregnant or breast feeding,

ask a health professional before use

Keep out of reach of children.

In case of overdose, get medical help or contact a Poison Control Center right away.

Directions

- swallow with water, do not chew
- adults and children 12 years and over:
- 2 softgels every ½ hour or 4 softgels every hour as needed for diarrhea
- 2 softgels every ½ hour to 1 hour as needed for overindulgence (upset stomach, heartburn, indigestion, nausea)
- do not exceed 16 softgels in 24 hours
- use until diarrhea stops but not more than 2 days
- children under 12 years: ask a doctor
- drink plenty of clear fluids to help prevent dehydration caused by diarrhea

Other information

- each softgel contains:
- salicylate 102 mg
- low sodium
- do not exceed 25°C